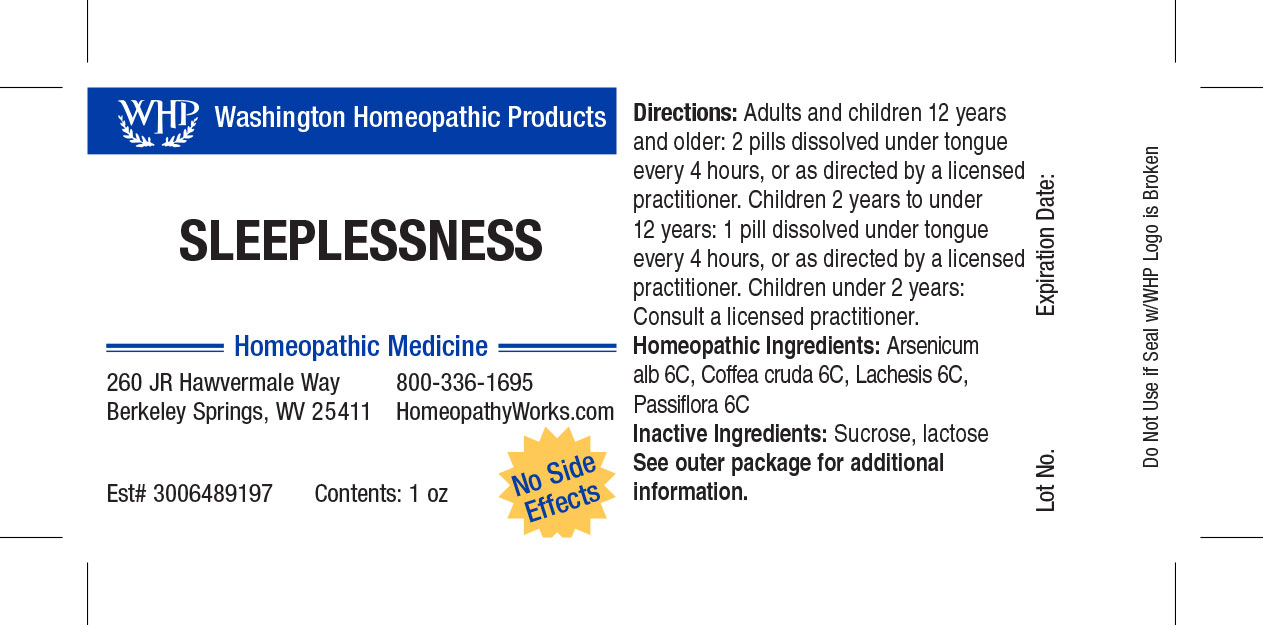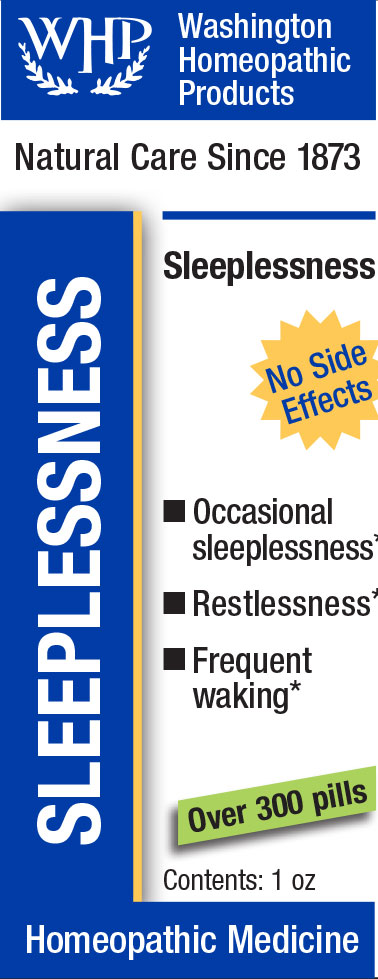 DRUG LABEL: WHP Sleeplessness
NDC: 71919-803 | Form: PELLET
Manufacturer: Washington Homeopathic Products
Category: homeopathic | Type: HUMAN OTC DRUG LABEL
Date: 20250128

ACTIVE INGREDIENTS: PASSIFLORA INCARNATA FLOWERING TOP 6 [hp_C]/1 1; ARABICA COFFEE BEAN 6 [hp_C]/1 1; ARSENIC TRIOXIDE 6 [hp_C]/1 1; LACHESIS MUTA VENOM 6 [hp_C]/1 1
INACTIVE INGREDIENTS: SUCROSE; LACTOSE

WHP Sleeplessness

ACTIVE INGREDIENTS

ARSENICUM ALB 6C

COFFEA CRUDA 6C

LACHESIS 6C

PASSIFLORA 6C

USES

Temporarily eases occasional sleeplessness.

KEEP OUT OF REACH OF CHILDREN

As with all medications, keep out of reach of children.

INDICATIONS

ARSENICUM ALB Vomiting

COFFEA CRUDA Sleeplessness

LACHESIS Sore throat

PASSIFLORA Sleeplessness

STOP USE AND ASK DOCTOR

If symptoms persist or recur, discontinue use. If pregnant or nursing, consult a licensed practitioner before using this product.

INACTIVE INGREDIENTS

Sucrose/Lactose

DIRECTIONS

Directions: Adults and children 12 years and older: 2 pills dissolved under tongue every 4 hours, or as directed by a licensed practitioner. Children 4 years to under 12 years: 1 pill dissolved under tongue every 4 hours, or as directed by a licensed practitioner. Children under 4 years: Consult a licensed practitioner.